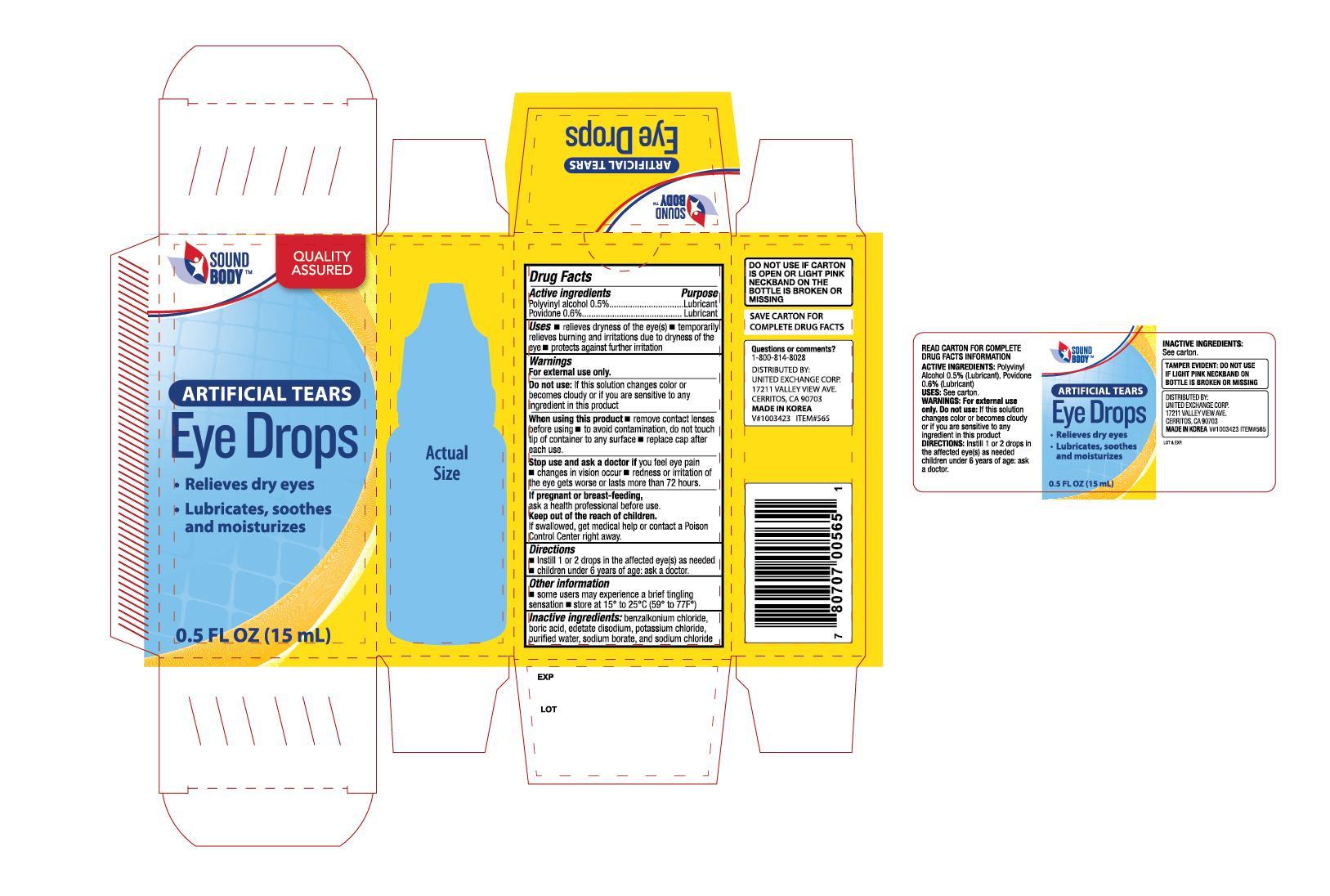 DRUG LABEL: Sound Body Artificial Tears
NDC: 65923-565 | Form: SOLUTION/ DROPS
Manufacturer: United Exchange Corp.
Category: otc | Type: HUMAN OTC DRUG LABEL
Date: 20140225

ACTIVE INGREDIENTS: POLYVINYL ALCOHOL 5 mg/1 mL; POVIDONE 6 mg/1 mL
INACTIVE INGREDIENTS: BENZALKONIUM CHLORIDE; BORIC ACID; EDETATE DISODIUM; POTASSIUM CHLORIDE; WATER; SODIUM BORATE; SODIUM CHLORIDE

Active ingredients Purpose

Polyvinyl alcohol 0.5%..................................... Lubricant

Povidone 0.6%............................................... Lubricant

Uses

- relieves dryness of the eye(s)
- temporarily relieves burning and irritations due to dryness of the eye
- protects against further irritation

Warnings

For external use only

Do not use: if this solution changes color or becoems cloudy or if you are sensitive to any ingredient in this product

When using this product

- remove contact lenses before using
- to avoid contamination, do not touch tip of container to any surface
- replace cap after each use

Stop use and ask a doctor if you feel eye pain

- changes in vision occur
- redness or irritation of the eye gets worse or lasts more than 72 hours

PREGNANCY OR BREAST FEEDING

If pregnant or breast-feeding, ask a health professional before use

Keep out of the reach of children.

If swallowed, get medical help or contact a Poison Control Center right away.

Directions

- Instill 1 or 2 drops in the affected eye(s) as needed
- children under 6 years of age; ask a doctor

Other information

- some users may experience a brief tingling sensation
- store at 15° to 25°C (59° to 77°F)

INACTIVE INGREDIENT

Inactive ingredients: benzalkonium chloride, boric acid, edetate disodium, potassium chloride, purified water, sodium borate, and sodium chloride

DOSAGE AND ADMINISTRATION

DISTRIBUTED BY:

UNITED EXCHANGE CORP.

17211 VALLEY VIEW AVE.

CERRITOS, CA 90703 USA